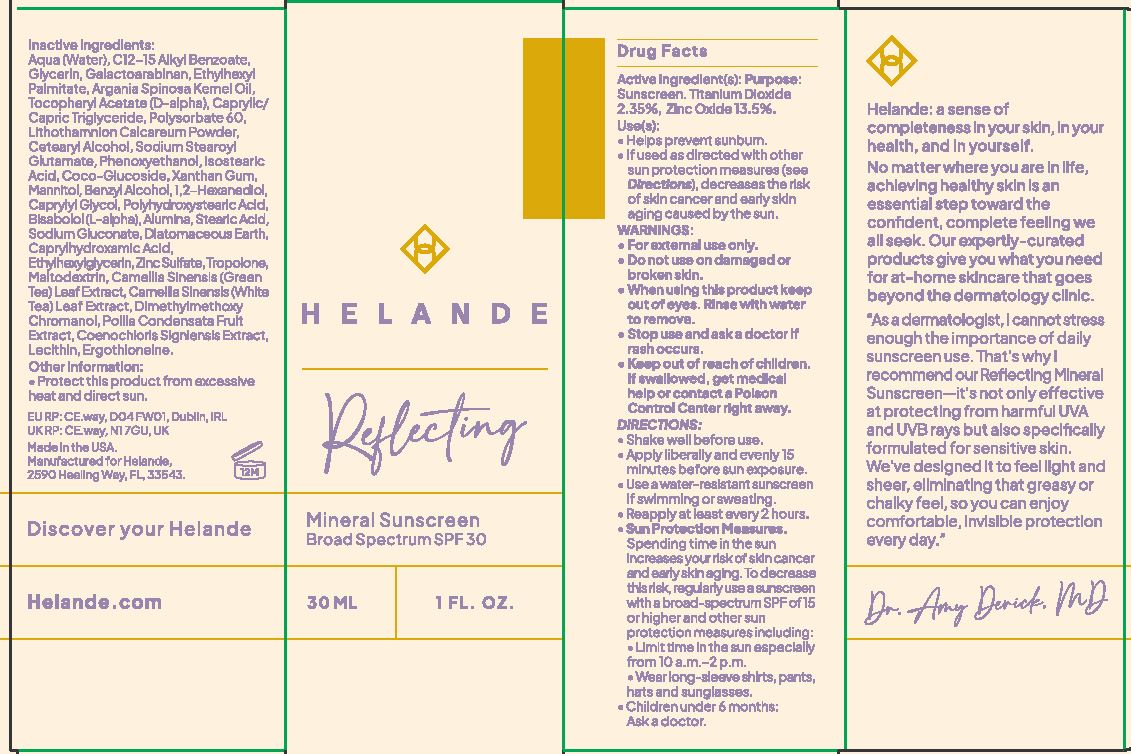 DRUG LABEL: Reflecting Mineral Sunscreen
NDC: 85767-610 | Form: LOTION
Manufacturer: Helande, LLC
Category: otc | Type: HUMAN OTC DRUG LABEL
Date: 20250611

ACTIVE INGREDIENTS: ZINC OXIDE 0.135 g/100 mL; TITANIUM DIOXIDE 0.023 g/100 mL
INACTIVE INGREDIENTS: POLYSORBATE 60; ETHYLHEXYL PALMITATE; 1,2-HEXANEDIOL; PHYMATOLITHON CALCAREUM; DIMETHYLMETHOXY CHROMANOL; POLLIA CONDENSATA FRUIT; ISOSTEARIC ACID; COENOCHLORIS SIGNIENSIS; DIATOMACEOUS EARTH; COCO-GLUCOSIDE; ALPHA-TOCOPHEROL ACETATE; GLYCERIN; LECITHIN, SOYBEAN; ERGOTHIONEINE; ZINC SULFATE; GREEN TEA LEAF; MALTODEXTRIN; SODIUM GLUCONATE; WATER; GALACTOARABINAN; CAPRYLHYDROXAMIC ACID; ALKYL (C12-15) BENZOATE; ARGANIA SPINOSA KERNEL OIL; CETEARYL ALCOHOL; SODIUM STEAROYL GLUTAMATE; MANNITOL; ALUMINA; XANTHAN GUM; CAPRYLYL GLYCOL; STEARIC ACID; TROPOLONE; BENZYL ALCOHOL; BISABOLOL; CAPRYLIC/CAPRIC TRIGLYCERIDE; POLYHYDROXYSTEARIC ACID (2300 MW); PHENOXYETHANOL; ETHYLHEXYLGLYCERIN

Active Ingredient(s)

Titanium Dioxide 2.35%, Zinc Oxide 13.5%

Purpose:

Sunscreen.

WARNINGS

Keep out of reach of children. If swallowed, get medical help or contact a Poison Control Center right away.

Use(s):

- Helps prevent sunburn.
- If used as directed with other sun protection measures (see Directions), decreases the risk of skin cancer and early skin aging caused by the sun.

WARNINGS:

- For external use only.
- Do not use on damaged or broken skin.
- When using this product keep out of eyes. Rinse with water to remove.
- Stop use and ask a doctor if rash occurs.
- Keep out of reach of children. If swallowed, get medical help or contact a Poison Control Center right away.

DIRECTIONS:

- Shake well before use.
- Apply liberally and evenly 15 minutes before sun exposure.
- Use a water-resistant sunscreen if swimming or sweating.
- Reapply at least every 2 hours.
- Sun Protection Measures.

Spending time in the sun increases your risk of skin cancer and early skin aging. To decrease this risk, regularly use a sunscreen with a broad-spectrum SPF of 15 or higher and other sun protection measures including:

- Limit time in the sun especially from 10a.m.-2p.m.
- Wear long-sleeve shirts, pants, hats and sunglasses
- Children under 6 months: Ask a doctor.

Inactive Ingredients:

Aqua (Water), C12-15 Alkyl Benzoate, Glycerin, Galactoarabinan, Ethylhexyl Palmitate, Argania Spinosa Kernel Oil, Tocopheryl Acetate (D-alpha), Caprylic/Capric Triglyceride, Polysorbate 60, Lithothamnion Calcareum Powder, Cetearyl Alcohol, Sodium Stearoyl Glutamate, Phenoxyethanol, Isostearic Acid, Coco-Glucoside, Xanthan Gum, Mannitol, Benzyl Alcohol, 1,2-Hexanediol, Caprylyl Glycol, Polyhydroxystearic Acid, Bisabolol (L-alpha), Alumina, Stearic Acid, Sodium Gluconate, Diatomaceous Earth, Caprylhydroxamic Acid, Ethylhexylglycerin, Zinc Sulfate, Tropolone, Maltodextrin, Camellia Sinensis (Green Tea) Leaf Extract, Camellia Sinensis (White Tea) Leaf Extract, Dimethylmethoxy Chromanol, Pollia Condensata Fruit Extract, Coenochloris Signiensis Extract, Lecithin, Ergothioneine

Other Information:

- Protect this product from excessive heat and direct sun.